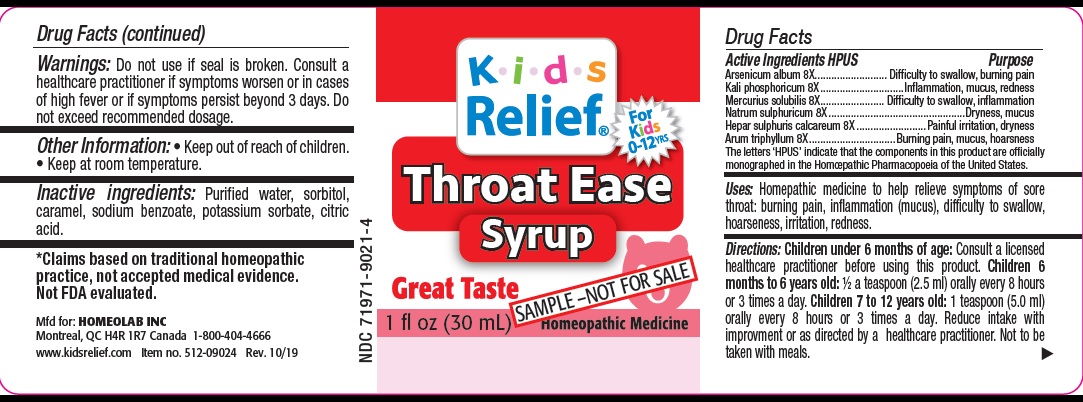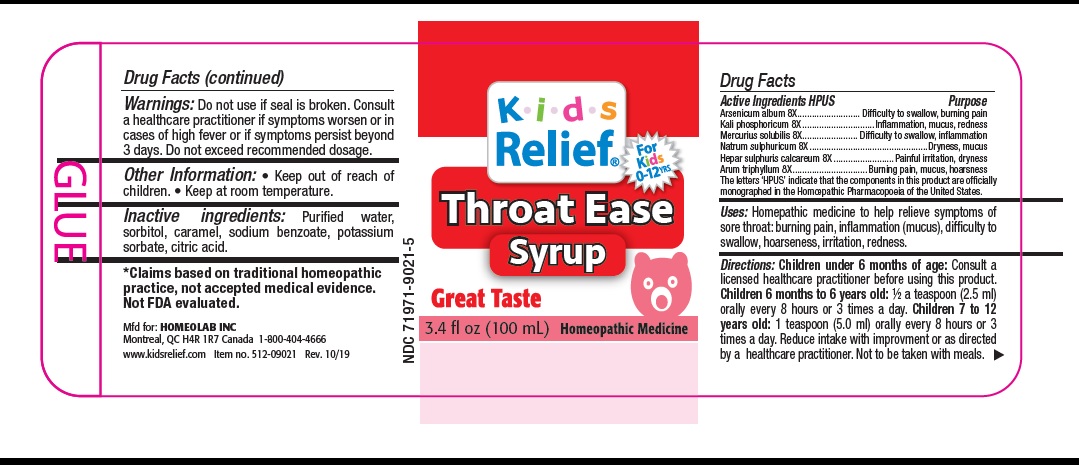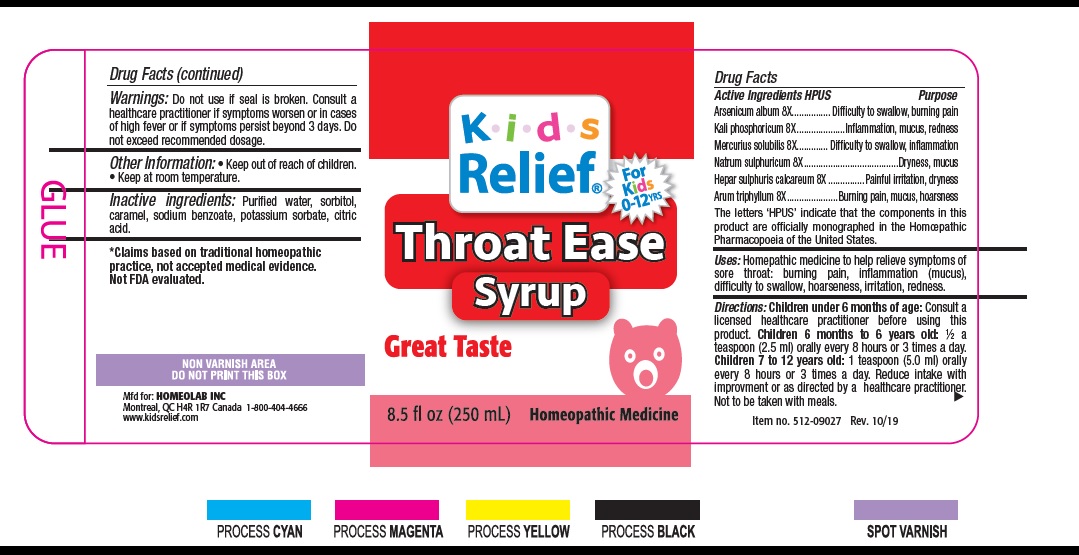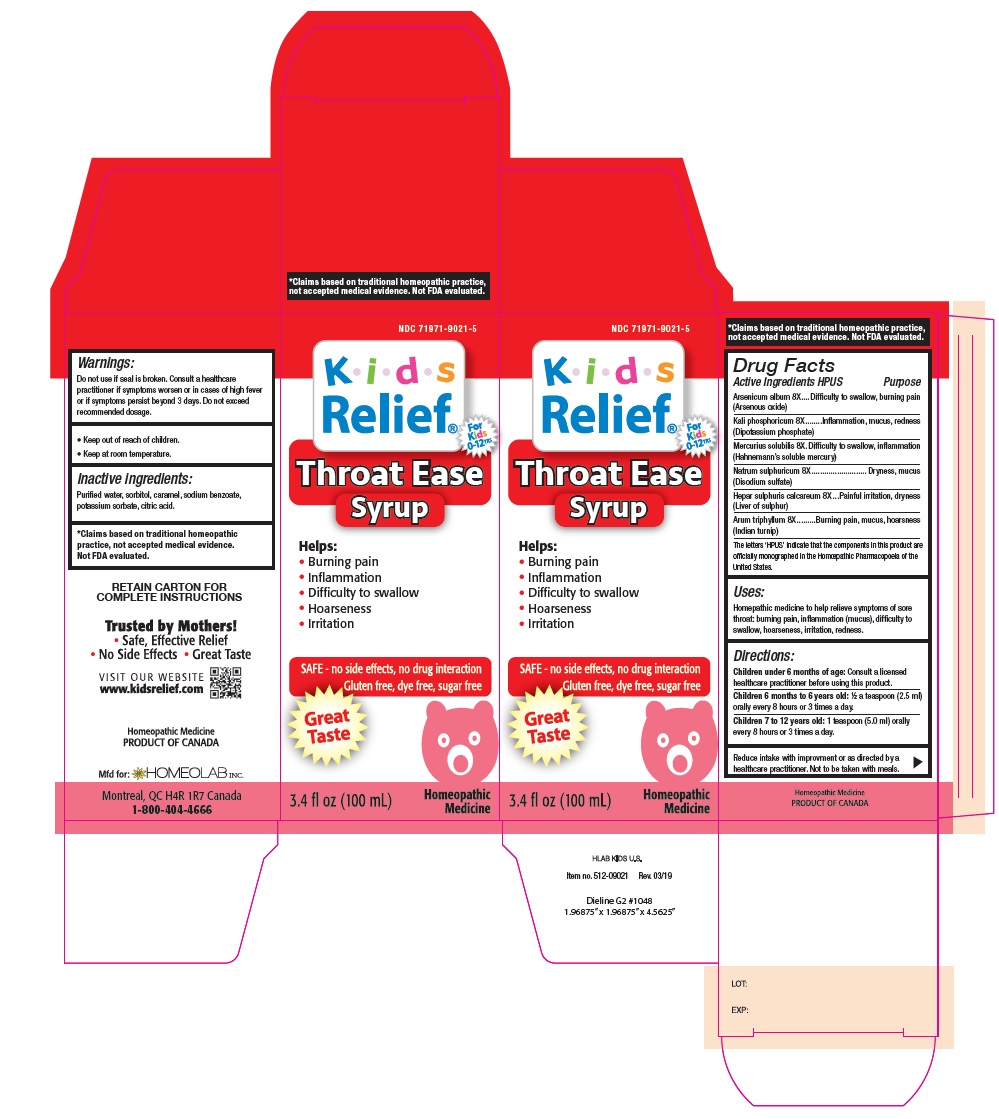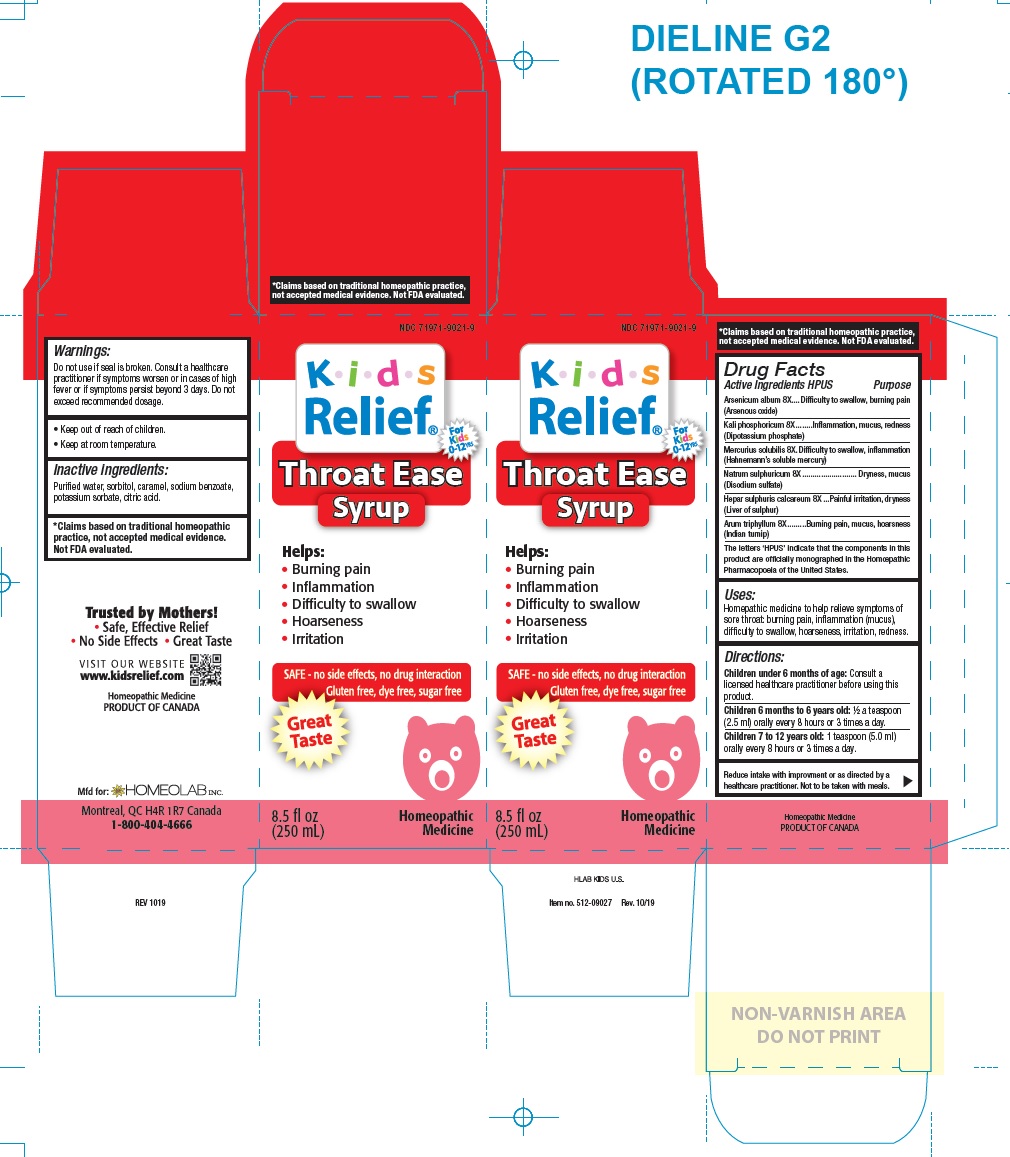 DRUG LABEL: Kids Relief
NDC: 71971-9021 | Form: LIQUID
Manufacturer: Homeolab International (Canada) inc
Category: homeopathic | Type: HUMAN OTC DRUG LABEL
Date: 20191023

ACTIVE INGREDIENTS: ARSENIC TRIOXIDE 8 [hp_X]/100 mL; DIBASIC POTASSIUM PHOSPHATE 8 [hp_X]/100 mL; MERCURIUS SOLUBILIS 8 [hp_X]/100 mL; SODIUM SULFATE 8 [hp_X]/100 mL; CALCIUM SULFIDE 8 [hp_X]/100 mL; ARISAEMA TRIPHYLLUM ROOT 8 [hp_X]/100 mL
INACTIVE INGREDIENTS: WATER; SORBITOL; SODIUM BENZOATE; POTASSIUM SORBATE; CITRIC ACID MONOHYDRATE; CARAMEL

Active Ingredients HPUS:

Arsenicum Album (Arsenous Oxide) 8X

Kali Phosphoricum (Dipotassium phosphate) 8X

Mercuris Solubilis (Hahnemann’s soluble mercury) 8X

Natrum Sulphuricum (Disodium sulfate) 8X

Hepar Sulphuris Calcareum (Liver of sulfur) 8X

Arum Triphyllum (Indian turnip) 8X

Purpose :

Homeopathic remedy helps relieve symptoms of sore throat, burning pain, inflammation (mucus), difficulty to swallow, hoarseness and irritation.

The letters 'HPUS' indicate that the components in this product are officially monographed in the Homoeopathic Pharmacopoeia of the United States.

*Claims based on traditional homeopathic practice, not accepted medical evidence. Not FDA evaluated

Uses :

This homeopathic medicine to help relieve sore throat symptoms:
• burning pain
• inflammation
• difficulty to swallow
• hoarseness
• irritation

Warnings

Do not use if seal is broken or missing.
Stop use and ask a doctor in cases of high fever or if symptoms worsen or persist for more than 3 days.
Keep out of reach of children.

Directions

Children under 6 months of age: Consult a licensed healthcare practitioner before using this product.

Children 6 months to 6 years old: ½ a teaspoon (2.5 ml) orally every 8 hours or 3 times a day.

Children 7 to 12 years old: 1 teaspoon (5.0 ml) orally every 8 hours or 3 times a day.

Reduce intake with improvements.

Not to be taken with meals

Keep out of reach of children.

Other information

•Store at room temperature

Inactive ingredients

Purified water, sorbitol, sodium benzoate, potassium sorbate, citric acid, caramel.